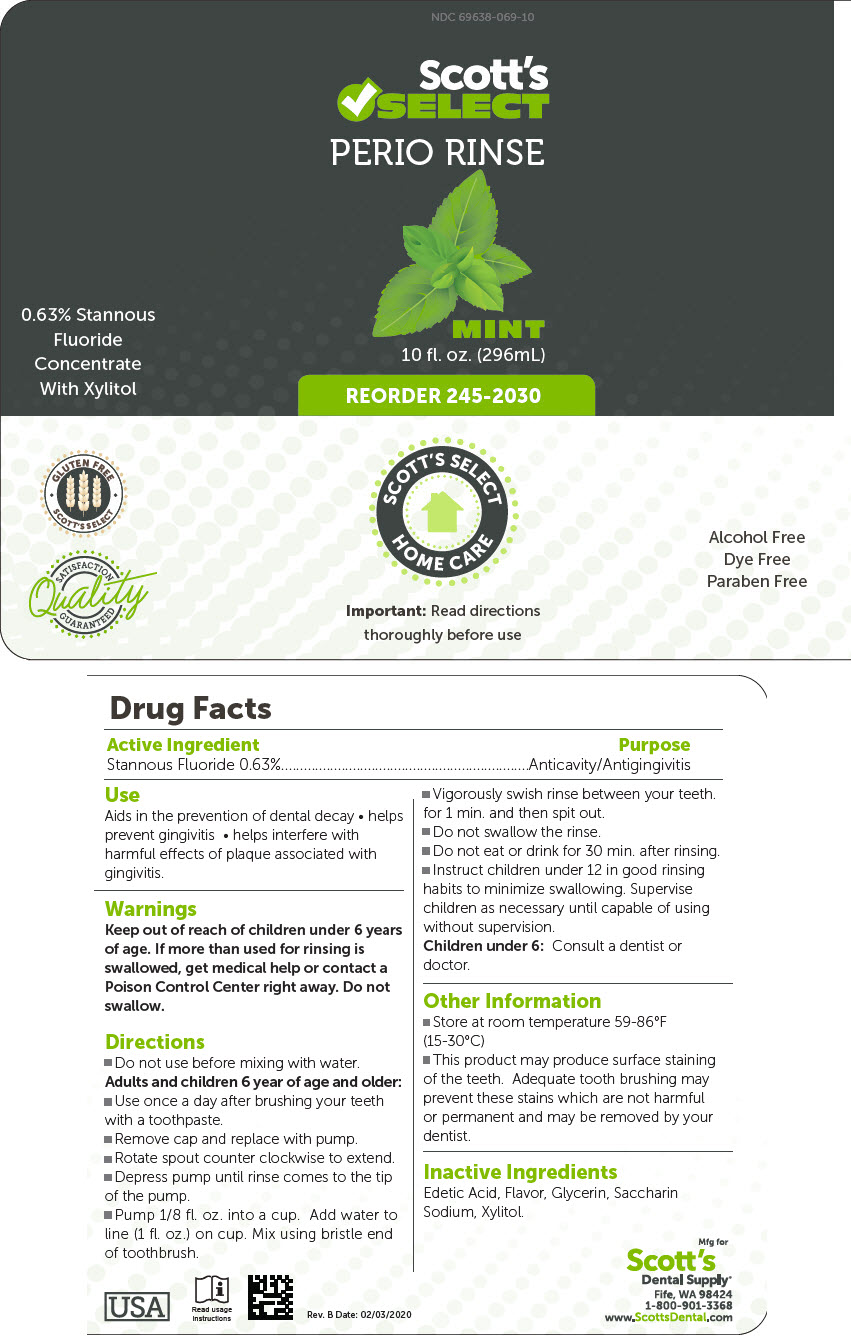 DRUG LABEL: Scotts Select Perio Rinse Stannous Fluoride
NDC: 69638-069 | Form: MOUTHWASH
Manufacturer: Scott's Dental Supply LLC
Category: otc | Type: HUMAN OTC DRUG LABEL
Date: 20220809

ACTIVE INGREDIENTS: STANNOUS FLUORIDE 0.63 mg/100 mL
INACTIVE INGREDIENTS: EDETIC ACID; GLYCERIN; SACCHARIN SODIUM; XYLITOL

Scott's Select Perio Rinse .63% Stannous Fluoride

Drug Facts

Active Ingredient

Stannous Fluoride 0.63%

Purpose

Anticavity/Antigingivitis

Use

Aids in the prevention of dental decay

- helps prevent gingivitis
- helps interfere with harmful effects of plaque associated with gingivitis.

Warnings

Keep out of reach of children under 6 years of age. If more than used for rinsing is swallowed, get medical help or contact a Poison Control Center right away. Do not swallow.

Directions

- Do not use before mixing with water.

Adults and children 6 year of age and older:

- Use once a day after brushing your teeth with a toothpaste.
- Remove cap and replace with pump.
- Rotate spout counter clockwise to extend.
- Depress pump until rinse comes to the tip of the pump.
- Pump 1/8 fl. oz. into a cup. Add water to line (1 fl. oz.) on cup. Mix using bristle end of toothbrush.
- Vigorously swish rinse between your teeth. for 1 min. and then spit out.
- Do not swallow the rinse.
- Do not eat or drink for 30 min. after rinsing.
- Instruct children under 12 in good rinsing habits to minimize swallowing. Supervise children as necessary until capable of using without supervision.

Children under 6: Consult a dentist or doctor.

Other Information

- Store at room temperature 59-86°F (15-30°C)
- This product may produce surface staining of the teeth. Adequate tooth brushing may prevent these stains which are not harmful or permanent and may be removed by your dentist.

Inactive Ingredients

Edetic Acid, Flavor, Glycerin, Saccharin Sodium, Xylitol.

PRINCIPAL DISPLAY PANEL - 296 mL Bottle Label

NDC 69638-069-10

Scott's
✔SELECT
PERIO RINSE

0.63% Stannous
Fluoride
Concentrate
With Xylitol

MINT

10 fl. oz. (296mL)

REORDER 245-2030

GLUTEN FREE
SCOTT'S SELECT

SCOTT'S SELECT
HOME CARE

Alcohol Free
Dye Free
Paraben Free

SATISFACTION
Quality
GUARANTEED

Important: Read directions
thoroughly before use